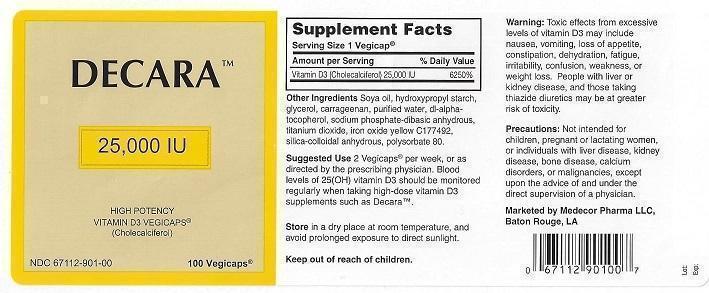 DRUG LABEL: DECARA HIGH POTENCY VITAMIN D3
NDC: 67112-901 | Form: CAPSULE
Manufacturer: Medecor Pharma, LLC
Category: other | Type: Dietary Supplement
Date: 20221227

ACTIVE INGREDIENTS: CHOLECALCIFEROL 25000 [iU]/1 1
INACTIVE INGREDIENTS: SOYBEAN OIL; HYDROXYPROPYL CORN STARCH (5% SUBSTITUTION BY WEIGHT); GLYCERIN; CARRAGEENAN; WATER; TOCOPHEROL; SODIUM PHOSPHATE, DIBASIC, ANHYDROUS; TITANIUM DIOXIDE; FERRIC OXIDE YELLOW; SILICON DIOXIDE; POLYSORBATE 80

MEDECOR PHARMA - DECARA HIGH POTENCY VITAMIN D3 (67112-901)

STATEMENT OF IDENTITY

VITAMIN D3 (CHOLECALCIFEROL) 25,000 IU